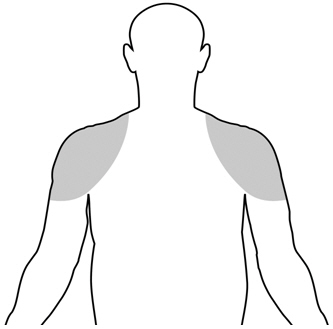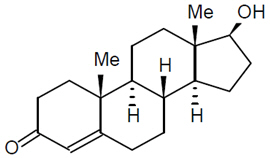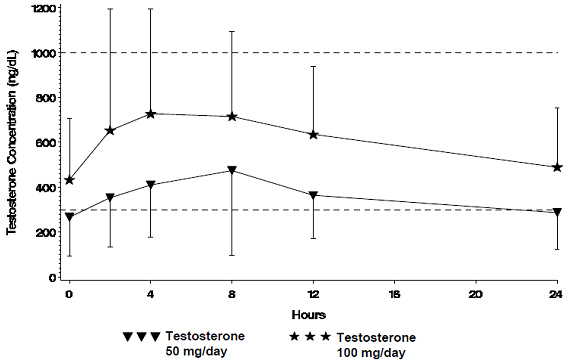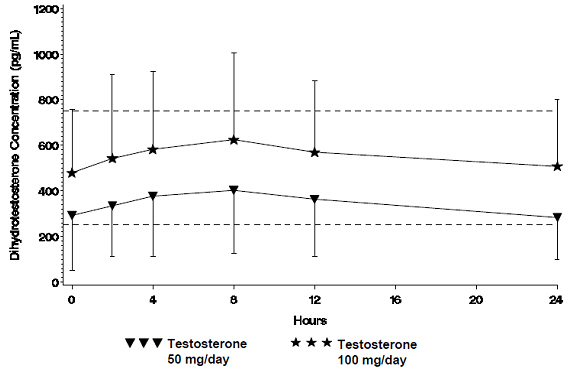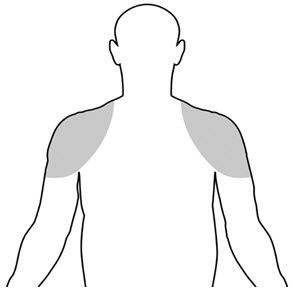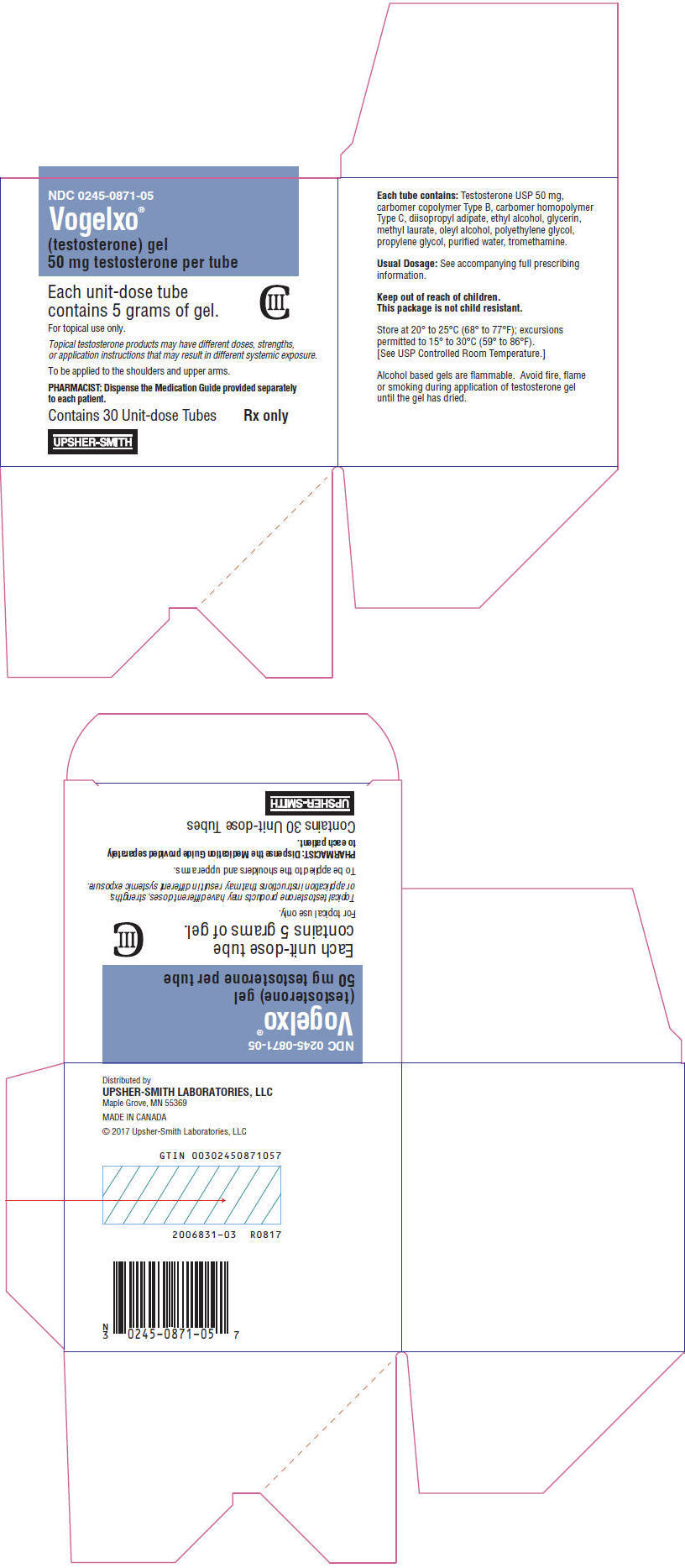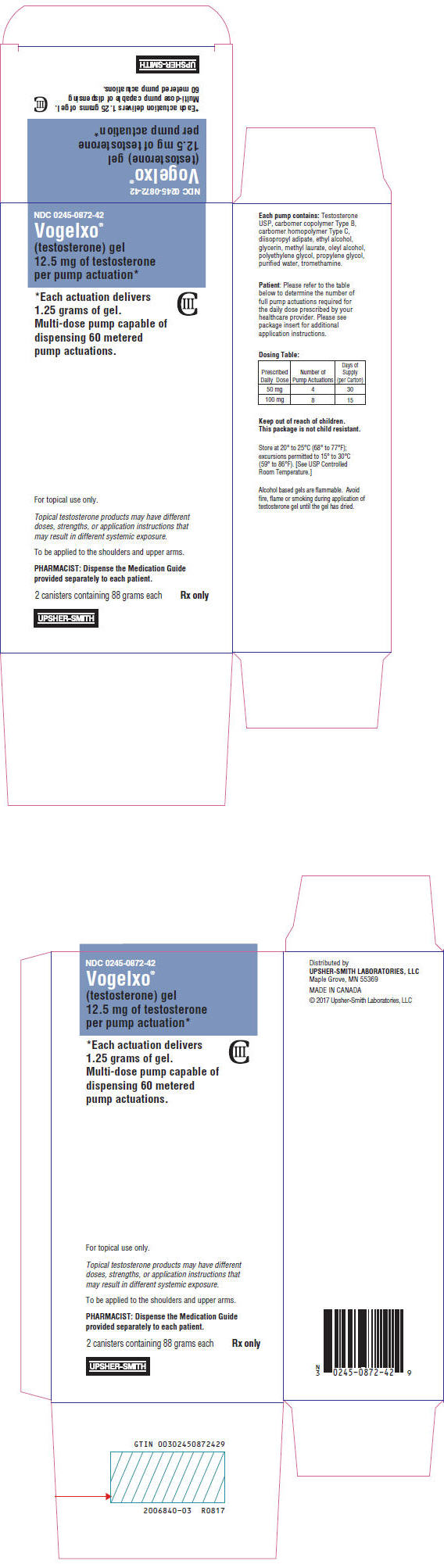 DRUG LABEL: Vogelxo
NDC: 0245-0871 | Form: GEL
Manufacturer: Upsher-Smith Laboratories, LLC
Category: prescription | Type: HUMAN PRESCRIPTION DRUG LABEL
Date: 20250714
DEA Schedule: CIII

ACTIVE INGREDIENTS: TESTOSTERONE 50 mg/5 g
INACTIVE INGREDIENTS: CARBOMER COPOLYMER TYPE B (ALLYL PENTAERYTHRITOL CROSSLINKED); CARBOMER HOMOPOLYMER TYPE C (ALLYL PENTAERYTHRITOL CROSSLINKED); DIISOPROPYL ADIPATE; ALCOHOL; GLYCERIN; METHYL LAURATE; OLEYL ALCOHOL; POLYETHYLENE GLYCOL, UNSPECIFIED; PROPYLENE GLYCOL; WATER; TROMETHAMINE

HIGHLIGHTS OF PRESCRIBING INFORMATION

These highlights do not include all the information needed to use VOGELXO safely and effectively. See full prescribing information for VOGELXO.
VOGELXO®(testosterone) gel, for topical use, CIII
Initial U.S. Approval: 1953

WARNING: SECONDARY EXPOSURE TO TESTOSTERONE

See full prescribing information for complete boxed warning

- Virilization has been reported in children who were secondarily exposed to testosterone gel. (5.2, 6.2)
- Children should avoid contact with unwashed or unclothed application sites in men using testosterone gel. (2.2, 5.2)
- Healthcare providers should advise patients to strictly adhere to recommended instructions for use. (2.2, 5.2, 17)

RECENT MAJOR CHANGES

Contraindications (4) | 04/2020

1 INDICATIONS AND USAGE

Vogelxo is an androgen indicated for testosterone replacement therapy in males for conditions associated with a deficiency or absence of endogenous testosterone:

- Primary hypogonadism (congenital or acquired). (1)
- Hypogonadotropic hypogonadism (congenital or acquired). (1)

Limitations of Use:

- Safety and efficacy of Vogelxo in men with age-related hypogonadism have not been established (1)
- Safety and efficacy of Vogelxo in males less than 18 years old have not been established (8.4)
- Topical testosterone products may have different doses, strengths, or application instructions that may result in different systemic exposure (1, 12.3)

2 DOSAGE AND ADMINISTRATION

- Prior to initiating Vogelxo, confirm the diagnosis of hypogonadism by ensuring that serum testosterone has been measured in the morning on at least two separate days and that these concentrations are below the normal range (2).
- Recommended starting dose for adult males: 50 mg of testosterone (one tube or one packet or 4 pump actuations) applied topically once daily at approximately the same time each day. (2.1)
- Apply to clean, dry, intact skin of the shoulders and/or upper arms. Do not apply Vogelxo to the genitals or abdomen. (2.1, 2.2)
- If morning pre-dose serum testosterone concentration is below the normal range, increase dose to 100 mg. (2.1)
- Pre-dose serum testosterone concentration should be assessed periodically. (2.1)
- Patients should wash hands with soap and water immediately after applying Vogelxo and cover application site(s) with clothing after gel has dried. Wash the application sites thoroughly with soap and water prior to any situation where skin-to-skin contact of the application site with another person is anticipated. (2.2)

3 DOSAGE FORMS AND STRENGTHS

Topical Gel available as:

- 50 mg of testosterone in a unit-dose tube. (3)
- 50 mg of testosterone in a unit-dose packet. (3)
- 12.5 mg of testosterone per one pump actuation in a metered-dose pump. (3)

4 CONTRAINDICATIONS

- Men with known carcinoma of the breast or known or suspected carcinoma of the prostate. (4, 5.1)
- Women who are pregnant. Testosterone may cause fetal harm. (4, 8.1)

5 WARNINGS AND PRECAUTIONS

- Monitor patients with benign prostatic hyperplasia (BPH) for worsening of signs and symptoms of BPH. (5.1)
- Avoid unintentional exposure of women or children to Vogelxo. Secondary exposure to testosterone can produce signs of virilization. Vogelxo should be discontinued until the cause of virilization is identified. (5.2)
- Venous thromboembolism (VTE), including deep vein thrombosis (DVT) and pulmonary embolism (PE), have been reported in patients using testosterone products. Evaluate patients with signs or symptoms consistent with DVT or PE. (5.4)
- Some postmarketing studies have shown an increased risk of myocardial infarction and stroke associated with use of testosterone replacement therapy. (5.5)
- Exogenous administration of androgens may lead to azoospermia. (5.8)
- Edema, with or without congestive heart failure, may be a complication in patients with preexisting cardiac, renal, or hepatic disease. (5.10)
- Sleep apnea may occur in those with risk factors. (5.12)
- Monitor prostate specific antigen (PSA), hematocrit, and lipid concentrations periodically. (5.1, 5.3, 5.13)
- Vogelxo is flammable until dry. (5.16)

6 ADVERSE REACTIONS

- Most common adverse reactions (incidence ≥ 2% of the testosterone gel patients and greater than placebo) are application site reactions and increased hematocrit. (6.1)

To report SUSPECTED ADVERSE REACTIONS, contact UPSHER-SMITH LABORATORIES, LLC at 1-855-899-9180 or FDA at 1-800-FDA-1088 or www.fda.gov/medwatch.

7 DRUG INTERACTIONS

- Androgens may decrease blood glucose and therefore may decrease insulin requirements in diabetic patients. (7.1)
- Changes in anticoagulant activity may be seen with androgens. More frequent monitoring of International Normalized Ratio (INR) and prothrombin time is recommended in patients taking warfarin. (7.2)
- Use of testosterone with corticosteroids may result in increased fluid retention. Use with caution, particularly in patients with cardiac, renal or hepatic disease. (7.3)

8 USE IN SPECIFIC POPULATIONS

Geriatric Patients: There are insufficient long-term safety data to assess the potential risks of cardiovascular disease and prostate cancer. (8.5)

FULL PRESCRIBING INFORMATION

WARNING: SECONDARY EXPOSURE TO TESTOSTERONE

- Virilization has been reported in children who were secondarily exposed to testosterone gel [see Warnings and Precautions (5.2)and Adverse Reactions (6.2)] .
- Children should avoid contact with unwashed or unclothed application sites in men using testosterone gel [see Dosage and Administration (2.2)and Warnings and Precautions (5.2)] .
- Healthcare providers should advise patients to strictly adhere to recommended instructions for use [see Dosage and Administration (2.2), Warnings and Precautions (5.2)and Patient Counseling Information (17)] .

1 INDICATIONS AND USAGE

Vogelxo is indicated for replacement therapy in adult males for conditions associated with a deficiency or absence of endogenous testosterone:

- Primary hypogonadism (congenital or acquired): testicular failure due to cryptorchidism, bilateral torsion, orchitis, vanishing testis syndrome, orchiectomy, Klinefelter's syndrome, chemotherapy, or toxic damage from alcohol or heavy metals. These men usually have low serum testosterone levels and gonadotropins (follicle-stimulating hormone [FSH], luteinizing hormone [LH]) above the normal range.
- Hypogonadotropic hypogonadism (congenital or acquired): gonadotropin or luteinizing hormone-releasing hormone (LHRH) deficiency or pituitary-hypothalamic injury from tumors, trauma, or radiation. These men have low testosterone serum levels but have gonadotropins in the normal or low range.

Limitations of Use:

- Safety and efficacy of Vogelxo in men with "age-related hypogonadism" (also referred to as "late-onset hypogonadism") have not been established.
- Safety and efficacy of Vogelxo in males less than 18 years old have not been established [see Use in Specific Populations (8.4)] .
- Topical testosterone products may have different doses, strengths, or application instructions that may result in different systemic exposure [see Dosage and Administration (2)and Clinical Pharmacology (12.3)] .

2 DOSAGE AND ADMINISTRATION

Prior to initiating Vogelxo, confirm the diagnosis of hypogonadism by ensuring that serum testosterone concentrations have been measured in the morning on at least two separate days and that these serum testosterone concentrations are below the normal range.

2.1 Dosing and Dose Adjustment

The recommended starting dose of Vogelxo is 50 mg of testosterone (one tube, one packet, or 4 pump actuations) applied topically once daily at approximately the same time each day to clean, dry intact skin of the shoulders and/or upper arms.

Dose Adjustment

To ensure proper dosing, serum testosterone concentrations should be measured. Morning, pre-dose serum testosterone concentrations should be measured approximately 14 days after initiation of therapy to ensure proper serum testosterone concentrations are achieved. If the serum testosterone concentration is below the normal range (300 ng/dL to 1,000 ng/dL), the daily Vogelxo dose may be increased from 50 mg testosterone (one tube, one packet, or 4 pump actuations) to 100 mg of testosterone (two tubes, two packets, or 8 pump actuations) once daily.

The maximum recommended dose of Vogelxo is 100 mg once daily.

2.2 Administration Instructions

Unit-Dose Tube or Packet

Upon opening the tube or packet the entire contents should be squeezed into the palm of the hand and immediately applied to the shoulders and/or upper arms (area of application should be limited to the area that will be covered by the patient's short sleeve t-shirt [ see figure below]).

Table 1 has specific dosing guidelines for when the unit-dose tubes or packets are used.

Table 1: Specific Dosing Guideline for Using the Unit-Dose Tubes or Packets
Prescribed Daily Dose | Number of Unit-Dose Tubes or Packets | Application Method
50 mg testosterone | One unit-dose tube or packet (once daily) | Apply one unit-dose tube or packet to one upper arm and shoulder.
100 mg testosterone | Two unit-dose tubes or packets (once daily) | Apply one unit-dose tube or packet to one upper arm and shoulder and then apply one unit-dose tube or packet to the opposite upper arm and shoulder.

Multi-Dose Metered Pump

Patients should be instructed to prime the pump before using it for the first time by fully depressing the pump mechanism (actuation) 3 times and discard this portion of the product to assure precise dose delivery. After the priming procedure, patients should completely depress the pump one time (actuation) for every 12.5 mg of testosterone required to achieve the daily prescribed dosage. Table 2 has specific dosing guidelines for when the metered pump is used.

Table 2: Specific Dosing Guidelines for Using the Multi-Dose Pump
Prescribed Daily Dose | Number of Pump Actuations | Application Method
50 mg testosterone | 4 (once daily) | Apply 4 pump actuations to one upper arm and shoulder
100 mg testosterone | 8 (once daily) | Apply 4 pump actuations to one upper arm and shoulder and then apply 4 pump actuations to the opposite upper arm and shoulder

The prescribed amount of product should be delivered directly into the palm of the hand and immediately applied to the shoulders and/or upper arms (area of application should be limited to the area that will be covered by the patient's short sleeve t-shirt [ see figure below]).

Do not apply Vogelxo to the genitals or to the abdomen.

Application sites should be allowed to dry completely prior to dressing.

Hands should be washed thoroughly with soap and water after Vogelxo has been applied.

Avoid fire, flame or smoking during the application of Vogelxo until the Vogelxo has dried [see Warnings and Precautions (5.2, 5.16)] .

In order to prevent transfer to another person, clothing should be worn to cover the application site(s). If direct skin-to-skin contact of the application site(s) with another person is anticipated, the application site(s) must be washed thoroughly with soap and water [see Warnings and Precautions (5.2)and Clinical Pharmacology (12.3)] .

The patient should avoid swimming or showering or washing the administration site for a minimum of 2 hours after application [see Clinical Pharmacology (12.3)] .

Strict adherence to the following precautions is advised in order to minimize the potential for secondary exposure to testosterone from Vogelxo treated skin:

- Children and women should avoid contact with unwashed or unclothed application site(s) of men using Vogelxo.
- Vogelxo should only be applied to the upper arms and shoulders. The area of application should be limited to the area that will be covered by a short sleeve t-shirt.
- Patients should wash their hands with soap and water immediately after applying Vogelxo.
- Patients should cover the application site(s) with clothing (e.g., a t-shirt) after the gel has dried.
- Prior to any situation in which direct skin-to-skin contact of the application site(s) with another person is anticipated, patients should wash the application site(s) thoroughly with soap and water to remove any testosterone residue.
- In the event that unwashed or unclothed skin to which Vogelxo has been applied comes in direct contact with the skin of another person, the general area of contact on the other person should be washed with soap and water as soon as possible.

3 DOSAGE FORMS AND STRENGTHS

Vogelxo (testosterone) gel is a clear to translucent hydroalcoholic topical gel for topical use available in unit-dose tubes, unit-dose packets, and multiple-dose metered pumps. Each tube or packet provides 50 mg testosterone in 5 g of gel. One pump actuation delivers 12.5 mg testosterone in 1.25 g of gel (4 actuations = 50 mg testosterone).

4 CONTRAINDICATIONS

- Vogelxo is contraindicated in men with carcinoma of the breast or known or suspected carcinoma of the prostate [see Warnings and Precautions (5.1)] .
- Vogelxo is contraindicated in women who are pregnant. Vogelxo can cause virilization of the female fetus when administered to a pregnant woman. Pregnant women need to be aware of the potential for skin transfer of testosterone from men treated with Vogelxo. If a pregnant woman is exposed to Vogelxo, she should be apprised of the potential hazard to the fetus [see Warnings and Precautions (5.2)and Use in Specific Populations (8.1)].

5 WARNINGS AND PRECAUTIONS

5.1 Worsening of Benign Prostatic Hyperplasia (BPH) and Potential Risk of Prostate Cancer

- Men with BPH treated with androgens are at an increased risk for worsening of signs and symptoms of BPH. Monitor patients with BPH for worsening signs and symptoms.
- Patients treated with androgens may be at increased risk for prostate cancer. Evaluate patients for prostate cancer prior to initiating and during treatment with androgens [see Contraindications (4)].

5.2 Potential for Secondary Exposure to Testosterone

Cases of secondary exposure resulting in virilization of children have been reported in postmarketing surveillance. Signs and symptoms have included enlargement of the penis or clitoris, development of pubic hair, increased erections and libido, aggressive behavior, and advanced bone age. In most cases, these signs and symptoms regressed with removal of the exposure to testosterone gel. In a few cases, however, enlarged genitalia did not fully return to age-appropriate normal size, and bone age remained modestly greater than chronological age. The risk of transfer was increased in some of these cases by not adhering to precautions for the appropriate use of the topical testosterone product. Children and women should avoid contact with unwashed or unclothed application sites in men using Vogelxo [see Dosage and Administration (2.2), Use in Specific Populations (8.1)and Clinical Pharmacology (12.3)] .

Inappropriate changes in genital size or development of pubic hair or libido in children, or changes in body hair distribution, significant increase in acne, or other signs of virilization in adult women should be brought to the attention of a physician and the possibility of secondary exposure to testosterone gel should also be brought to the attention of a physician. Testosterone gel should be promptly discontinued until the cause of virilization has been identified.

5.3 Polycythemia

Increases in hematocrit, reflective of increases in red blood cell mass, may require lowering or discontinuation of testosterone. Check hematocrit prior to initiating treatment. It would also be appropriate to re-evaluate the hematocrit 3 to 6 months after starting treatment, and then annually. If hematocrit becomes elevated, stop therapy until hematocrit decreases to an acceptable concentration. An increase in red blood cell mass may increase the risk of thromboembolic events.

5.4 Venous Thromboembolism

There have been postmarketing reports of venous thromboembolic events, including deep vein thrombosis (DVT) and pulmonary embolism (PE), in patients using testosterone products, such as Vogelxo. Evaluate patients who report signs and symptoms of pain, edema, warmth and erythema in the lower extremity for DVT and those who present with acute shortness of breath for PE. If a venous thromboembolic event is suspected, discontinue treatment with Vogelxo and initiate appropriate workup and management [see Adverse Reactions (6.2)] .

5.5 Cardiovascular Risk

Long term clinical safety trials have not been conducted to assess the cardiovascular outcomes of testosterone replacement therapy in men. To date, epidemiologic studies and randomized controlled trials have been inconclusive for determining the risk of major adverse cardiovascular events (MACE), such as non-fatal myocardial infarction, non-fatal stroke, and cardiovascular death, with the use of testosterone compared to non-use. Some studies, but not all, have reported an increased risk of MACE in association with use of testosterone replacement therapy in men. Patients should be informed of this possible risk when deciding whether to use or to continue to use Vogelxo.

5.6 Abuse of Testosterone and Monitoring of Serum Testosterone Concentrations

Testosterone has been subject to abuse, typically at doses higher than recommended for the approved indication and in combination with other anabolic androgenic steroids. Anabolic androgenic steroid abuse can lead to serious cardiovascular and psychiatric adverse reactions [see Drug Abuse and Dependence (9)] .

If testosterone abuse is suspected, check serum testosterone concentrations to ensure they are within therapeutic range. However, testosterone levels may be in the normal or subnormal range in men abusing synthetic testosterone derivatives. Counsel patients concerning the serious adverse reactions associated with abuse of testosterone and anabolic androgenic steroids. Conversely, consider the possibility of testosterone and anabolic androgenic steroid abuse in suspected patients who present with serious cardiovascular or psychiatric adverse events.

5.7 Use in Women

Due to lack of controlled evaluations in women and potential virilizing effects, Vogelxo is not indicated for use in women [see Contraindications (4)and Use in Specific Populations (8.1, 8.2)] .

5.8 Potential for Adverse Effects on Spermatogenesis

With large doses of exogenous androgens, including Vogelxo, spermatogenesis may be suppressed through feedback inhibition of pituitary follicle-stimulating hormone (FSH) which could possibly lead to adverse effects on semen parameters including sperm count.

5.9 Hepatic Adverse Effects

Prolonged use of high doses of orally active 17-alpha-alkyl androgens (e.g., methyltestosterone) has been associated with serious hepatic adverse effects (peliosis hepatis, hepatic neoplasms, cholestatic hepatitis, and jaundice). Peliosis hepatis can be a life-threatening or fatal complication. Long-term therapy with intramuscular testosterone enanthate, which elevate blood levels for prolonged periods, has produced multiple hepatic adenomas. Vogelxo is not known to produce these adverse effects. Nonetheless, patients should be instructed to report any signs or symptoms of hepatic dysfunction (e.g., jaundice). If these occur, promptly discontinue Vogelxo while the cause is evaluated.

5.10 Edema

Androgens, including Vogelxo, may promote retention of sodium and water. Edema, with or without congestive heart failure, may be a serious complication in patients with preexisting cardiac, renal, or hepatic disease. In addition to discontinuation of the drug, diuretic therapy may be required.

5.11 Gynecomastia

Gynecomastia occasionally develops and occasionally persists in patients being treated for hypogonadism [see Adverse Reactions (6.1)] .

5.12 Sleep Apnea

The treatment of hypogonadal men with testosterone may potentiate sleep apnea in some patients, especially those with risk factors such as obesity or chronic lung diseases.

5.13 Lipids

Changes in the serum lipid profile may occur. Monitor the lipid profile periodically, particularly after starting testosterone therapy and after any dose increases.

5.14 Hypercalcemia

Androgens, including Vogelxo, should be used with caution in cancer patients at risk of hypercalcemia (and associated hypercalciuria). Regular monitoring of serum calcium concentrations is recommended in these patients.

5.15 Decreased Thyroxine-binding Globulin

Androgens, including Vogelxo, may decrease concentrations of thyroxine-binding globulins, resulting in decreased total T4 serum concentrations and increased resin uptake of T3 and T4. Free thyroid hormone levels remain unchanged, however, and there is no clinical evidence of thyroid dysfunction.

5.16 Flammability

Alcohol-based products, including Vogelxo, are flammable; therefore, patients should be advised to avoid fire, flame or smoking until the Vogelxo has dried.

6 ADVERSE REACTIONS

6.1 Clinical Trial Experience

Because clinical trials are conducted under widely varying conditions, adverse reaction rates observed in the clinical trials of a drug cannot be directly compared to rates in the clinical trials of another drug and may not reflect the rates observed in practice.

In a controlled clinical study, 304 patients were treated with testosterone gel 50 mg or 100 mg or placebo gel for up to 90 days. Two hundred-five (205) patients received testosterone gel 50 mg or 100 mg daily and 99 patients received placebo. Subjects could be counted in both testosterone gel treatment groups if they received both 50 mg and 100 mg at different points in the study and experienced an adverse reaction at both dose levels. Adverse reactions reported by ≥1% of the testosterone gel patients and greater than placebo are listed in Table 3.

Table 3: Incidence of Adverse Reactions (Reported by ≥1% of the Testosterone Gel Patients and Greater than Placebo) in the Controlled Clinical Trial Through 90 Days
 | Testosterone Gel 50 mg | Testosterone Gel 100 mg | Placebo
Event | (n=103) | (n=149) | (n=99)
Application Site Reactions | 2% | 4% | 3%
Blood Pressure Increased | 1% | 1% | 0%
Gynecomastia | 1% | 0% | 0%
Headache | 1% | 1% | 0%
Hematocrit/Hemoglobin Increased | 1% | 2% | 0%
Hot Flushes | 1% | 0% | 0%
Insomnia | 1% | 0% | 0%
Mood Swings | 1% | 0% | 0%
Smell Disorder | 1% | 0% | 0%
Spontaneous Penile Erection | 1% | 0% | 0%
Taste Disorder | 1% | 1% | 0%

The following adverse reactions occurred in fewer than 1% of patients but were greater in testosterone gel groups compared to the placebo group: activated partial thromboplastin time prolonged, blood creatinine increased, prothrombin time prolonged, appetite increased, sensitive nipples, and acne.

In this clinical trial of testosterone gel, six patients had adverse events that led to their discontinuation. These events included: depression with suicidal ideation, urinary tract infection, mood swings and hypertension. No testosterone gel patients discontinued due to skin reaction. In one foreign Phase 3 trial, one subject discontinued due to a skin-related adverse event.

In the pivotal U.S. and European Phase 3 trials combined, at the 50 mg dosage strength, the percentage of subjects reporting clinically notable increases in hematocrit or hemoglobin were similar to placebo. However, in the 100 mg dose group, 2.3% and 2.8% of patients had a clinically notable increase in hemoglobin (≥ 19 g/dL) or hematocrit (≥ 58%), respectively, compared to 1.0% and 1.5% of patients in the placebo group, respectively.

In the combined U.S. and European open label extension studies, approximately 140 patients received testosterone gel for at least 6 months. The results from these studies are consistent with those reported for the U.S. controlled clinical trial.

6.2 Postmarketing Experience

The following adverse reactions have been identified during post-approval use of testosterone gel products. Because the reactions are reported voluntarily from a population of uncertain size, it is not always possible to reliably estimate their frequency or establish a causal relationship to drug exposure.

Secondary Exposure to Testosterone in Children

Cases of secondary exposure to testosterone resulting in virilization of children have been reported in postmarketing surveillance of testosterone gel products. Signs and symptoms of these reported cases have included enlargement of the clitoris (with surgical intervention) or of the penis, development of pubic hair, increased erections and libido, aggressive behavior, and advanced bone age. In most cases with a reported outcome, these signs and symptoms were reported to have regressed with removal of the testosterone gel exposure. In a few cases, however, enlarged genitalia did not fully return to age-appropriate normal size, and bone age remained modestly greater than chronological age. In some of the cases, direct contact with the sites of application on the skin of men using testosterone gel was reported. In at least one reported case, the reporter considered the possibility of secondary exposure from items such as the testosterone gel user's shirts and/or other fabrics, such as towels and sheets [see Warnings and Precautions (5.2)] .

Cardiovascular Disorders:

Myocardial infarction, stroke [see Warnings and Precautions (5.5)]

Vascular Disorders:

Venous thromboembolism [see Warnings and Precautions (5.4)].

7 DRUG INTERACTIONS

7.1 Insulin

Changes in insulin sensitivity or glycemic control may occur in patients treated with androgens. In diabetic patients, the metabolic effects of androgens may decrease blood glucose and, therefore, may necessitate a decrease in the dose of anti-diabetic medication.

7.2 Oral Anticoagulants

Changes in anticoagulant activity may be seen with androgens, therefore more frequent monitoring of international normalized ratio (INR) and prothrombin time are recommended in patients taking warfarin, especially at the initiation and termination of androgen therapy.

7.3 Corticosteroids

The concurrent use of testosterone with corticosteroids may result in increased fluid retention and requires careful monitoring particularly in patients with cardiac, renal or hepatic disease.

8 USE IN SPECIFIC POPULATIONS

8.1 Pregnancy

Risk Summary

Vogelxo is contraindicated in pregnant women. Testosterone is teratogenic and may cause fetal harm when administered to a pregnant woman based on data from animal studies and its mechanism of action [see Contraindications (4)and Clinical Pharmacology (12.1)] . Exposure of a female fetus to androgens may result in varying degrees of virilization. In animal developmental studies, exposure to testosterone in utero resulted in hormonal and behavioral changes in offspring and structural impairments of reproductive tissues in female and male offspring. These studies did not meet current standards for nonclinical development toxicity studies.

Data

Animal Data

In developmental studies conducted in rats, rabbits, pigs, sheep and rhesus monkeys, pregnant animals received intramuscular injection of testosterone during the period of organogenesis. Testosterone treatment at doses that were comparable to those used for testosterone replacement therapy resulted in structural impairments in both female and male offspring. Structural impairments observed in females included increased ano-genital distance, phallus development, empty scrotum, no external vagina, intrauterine growth retardation, reduced ovarian reserve, and increased ovarian follicular recruitment. Structural impairments seen in male offspring included increased or decreased testicular weight, larger seminal tubular lumen diameter, and higher frequency of occluded tubule lumen. Increased pituitary weight was seen in both sexes.

Testosterone exposure in uteroalso resulted in hormonal and behavioral changes in offspring. Hypertension was observed in pregnant female rats and their offspring exposed to doses approximately twice those used for testosterone replacement therapy.

8.2 Lactation

Risk Summary

Vogelxo is not indicated for use in women.

8.3 Females and Males of Reproductive Potential

Infertility

During treatment with large doses of exogenous androgens, including Vogelxo, spermatogenesis may be suppressed through feedback inhibition of the hypothalamic-pituitary-testicular axis [see Warnings and Precautions (5.8)] . Reduced fertility is observed in some men taking testosterone replacement therapy. Testicular atrophy, subfertility, and infertility have also been reported in men who abuse anabolic androgenic steroids [see Drug Abuse and Dependence (9.2)]. With either type of use, the impact on fertility may be irreversible.

8.4 Pediatric Use

The safety and efficacy of Vogelxo in pediatric patients less than 18 years old have not been established. Improper use may result in acceleration of bone age and premature closure of epiphyses.

8.5 Geriatric Use

There is insufficient long-term safety data in geriatric patients to assess the potentially increased risks of cardiovascular disease and prostate cancer [see Warnings and Precautions (5.1)] .

8.6 Renal Impairment

No studies were conducted in patients with renal impairment.

8.7 Hepatic Impairment

No studies were conducted in patients with hepatic impairment.

9 DRUG ABUSE AND DEPENDENCE

9.1 Controlled Substance

Vogelxo contains testosterone, a Schedule III controlled substance in the Controlled Substances Act.

9.2 Abuse

Drug abuse is intentional non-therapeutic use of a drug, even once, for its rewarding psychological and physiological effects. Abuse and misuse of testosterone are seen in male and female adults and adolescents. Testosterone, often in combination with other anabolic androgenic steroids (AAS), and not obtained by prescription through a pharmacy, may be abused by athletes and bodybuilders. There have been reports of misuse by men taking higher doses of legally obtained testosterone than prescribed and continuing testosterone despite adverse events or against medical advice.

Abuse-Related Adverse Reactions

Serious adverse reactions have been reported in individuals who abuse anabolic androgenic steroids and include cardiac arrest, myocardial infarction, hypertrophic cardiomyopathy, congestive heart failure, cerebrovascular accident, hepatotoxicity, and serious psychiatric manifestations, including major depression, mania, paranoia, psychosis, delusions, hallucinations, hostility and aggression.

The following adverse reactions have also been reported in men: transient ischemic attacks, convulsions, hypomania, irritability, dyslipidemias, testicular atrophy, subfertility, and infertility.

The following additional adverse reactions have been reported in women: hirsutism, virilization, deepening of voice, clitoral enlargement, breast atrophy, male-pattern baldness, and menstrual irregularities.

The following adverse reactions have been reported in male and female adolescents: premature closure of bony epiphyses with termination of growth, and precocious puberty.

Because these reactions are reported voluntarily from a population of uncertain size and may include abuse of other agents, it is not always possible to reliably estimate their frequency or establish a causal relationship to drug exposure.

9.3 Dependence

Behaviors Associated with Addiction

Continued abuse of testosterone and other anabolic steroids, leading to addiction is characterized by the following behaviors:

- Taking greater dosages than prescribed
- Continued drug use despite medical and social problems due to drug use
- Spending significant time to obtain the drug when supplies of the drug are interrupted
- Giving a higher priority to drug use than other obligations
- Having difficulty in discontinuing the drug despite desires and attempts to do so
- Experiencing withdrawal symptoms upon abrupt discontinuation of use

Physical dependence is characterized by withdrawal symptoms after abrupt drug discontinuation or a significant dose reduction of a drug. Individuals taking supratherapeutic doses of testosterone may experience withdrawal symptoms lasting for weeks or months which include depressed mood, major depression, fatigue, craving, restlessness, irritability, anorexia, insomnia, decreased libido and hypogonadotropic hypogonadism.

Drug dependence in individuals using approved doses of testosterone for approved indications has not been documented.

10 OVERDOSAGE

There were no reports of overdose in the testosterone gel clinical trials. There is a single report in the literature of acute overdosage after injection of testosterone enanthate. This subject had serum testosterone concentrations of up to 11,400 ng/dL, which were implicated in a cerebrovascular accident.

Treatment of overdosage would consist of discontinuation of Vogelxo, washing the application site with soap and water, and appropriate symptomatic and supportive care.

11 DESCRIPTION

Vogelxo (testosterone) gel, for topical use is a clear to translucent hydroalcoholic topical gel containing testosterone, an androgen. Vogelxo provides continuous transdermal delivery of testosterone for 24 hours, following a single application to intact, clean, dry skin of the shoulders and/or upper arms.

Vogelxo is available in unit-dose tubes, unit-dose packets, and a metered-dose pump. One 5-g or two 5-g tubes/packets of Vogelxo contains 50 mg or 100 mg of testosterone, respectively. One pump actuation dispenses 1.25 g of gel, which contains 12.5 mg of testosterone. Four pump actuations or eight pump actuations contain 50 mg or 100 mg of testosterone, respectively. Each metered-dose pump container is capable of dispensing 60 pump actuations.

The active pharmacological ingredient in Vogelxo is testosterone. Testosterone USP is a white to practically white crystalline powder chemically described as 17-β hydroxyandrost-4-en-3-one. The structural formula is shown in the following figure:

Inactive ingredients in Vogelxo are carbomer copolymer Type B, carbomer homopolymer Type C, diisopropyl adipate, ethyl alcohol, glycerin, methyl laurate, oleyl alcohol, polyethylene glycol, propylene glycol, purified water, and tromethamine.

12 CLINICAL PHARMACOLOGY

12.1 Mechanism of Action

Endogenous androgens, including testosterone and dihydrotestosterone (DHT) are responsible for the normal growth and development of the male sex organs and for maintenance of secondary sex characteristics. These effects include the growth and maturation of the prostate, seminal vesicles, penis, and scrotum; the development of male hair distribution, such as facial, pubic, chest, and axillary hair; laryngeal enlargement, vocal cord thickening, and alterations in body musculature and fat distribution.

Male hypogonadism, a clinical syndrome resulting from insufficient secretion of testosterone, has two main etiologies. Primary hypogonadism is caused by defects of the gonads, such as Klinefelter's syndrome or Leydig cell aplasia, whereas secondary hypogonadism is the failure of the hypothalamus (or pituitary) to produce sufficient gonadotropins (FSH, LH).

12.2 Pharmacodynamics

No specific pharmacodynamic studies were conducted using Vogelxo.

12.3 Pharmacokinetics

In a single-dose, replicate crossover clinical study evaluating 58 hypogonadal males, the serum testosterone exposures (AUC0-24and AUC0-t) and maximum testosterone concentration (Cmax) following a topical administration of 100 mg testosterone administration as a 2 × 5 g Vogelxo tubes (applied to the shoulders/upper arms) were bioequivalent to those following a topical administration of an approved testosterone gel product.

Absorption

Testosterone gel delivers physiologic amounts of testosterone, producing circulating testosterone concentrations that approximate normal levels (e.g., 300 – 1000 ng/dL) seen in healthy men.

The skin serves as a reservoir for the sustained release of testosterone into the systemic circulation. Approximately 10% of the testosterone applied on the skin surface is absorbed into the systemic circulation during a 24-hour period.

Single Dose

In a single dose, replicate crossover study, when Vogelxo 100 mg was applied, absorption of testosterone into the blood continued for the entire 24 hour dosing period. The average (± SD) AUC0-24and AUC0-tand Cmaxwere 6625 (±3671) ng∙hr/dL, 10425 (±5521) ng∙hr/dL, and 573 (±284) ng/dL, respectively.

Multiple Dose

With single daily applications of testosterone gel 50 mg and 100 mg, follow-up measurements at 30 and 90 days after starting treatment have confirmed that serum testosterone and DHT concentrations are generally maintained within the normal range.

Figure 1 summarizes the 24-hour pharmacokinetic profile of testosterone for patients maintained on testosterone gel 50 mg or testosterone gel 100 mg for 30 days.

Figure 1 Mean Steady-State Serum Testosterone (±SD) (ng/dL) Concentrations on Day 30 in Patients Applying Testosterone Once Daily

The average daily testosterone concentration produced by testosterone gel 100 mg at Day 30 was 612 (± 286) ng/dL and by testosterone gel 50 mg at Day 30 was 365 (± 187) ng/dL.

Distribution

Circulating testosterone is primarily bound in the serum to sex hormone-binding globulin (SHBG) and albumin. Approximately 40% of testosterone in plasma is bound to SHBG, 2% remains unbound (free) and the rest is loosely bound to albumin and other proteins.

Metabolism

Testosterone is metabolized to various 17-keto steroids through two different pathways. The major active metabolites of testosterone are estradiol and DHT. The average daily DHT concentration produced by testosterone gel 100 mg at Day 30 was 555 (± 293) pg/mL and by testosterone gel 50 mg at Day 30 was 346 (± 212) pg/mL.

Figure 2 summarizes the 24-hour pharmacokinetic profile of DHT for patients maintained on testosterone gel 50 mg or testosterone gel 100 mg for 30 days.

Figure 2 Mean Steady-State Serum Dihydrotestosterone (±SD) (pg/mL) Concentrations on Day 30 in Patients Applying Testosterone Once Daily

Excretion

There is considerable variation in the half-life of testosterone concentration as reported in the literature, ranging from 10 to 100 minutes. About 90% of a dose of testosterone given intramuscularly is excreted in the urine as glucuronic acid and sulfuric acid conjugates of testosterone and its metabolites. About 6% of a dose is excreted in the feces, mostly in the unconjugated form. Inactivation of testosterone occurs primarily in the liver.

Potential for Transfer from Male Patients to Female Partners

The potential for dermal testosterone transfer following Vogelxo use was evaluated in a clinical study between males dosed with Vogelxo and their untreated female partners. Two (2) hours after application of 50 mg of testosterone from 5 g of Vogelxo to upper arm and shoulder of one side by the male subjects, the couples (N = 48 couples) engaged in a 15 minute session of skin-to-skin contact. Serum concentrations of testosterone were monitored in the female subjects for 24 hours after the transfer procedure. Under these study conditions, unprotected female partners had a mean testosterone AUC0-24and Cmaxthat were 2.8 and 4 times greater than their mean baseline values, respectively. When a shirt covered the application site or the application site was washed, study results showed less than 10% increase in testosterone AUC0-24and Cmax, compared to baseline in these females.

Effect of Hand Washing

In a clinical study conducted to evaluate the effect of hand washing on the residual amount of testosterone, 36 healthy male subjects received 50 mg of testosterone from 5 g of Vogelxo on a hand and applied testosterone gel to the upper arm and shoulder of one side. Subjects washed their hands with liquid soap and warm water immediately after drug application. Then the hand was allowed to air dry or patted dry with a cloth towel. A skin swab sample was collected and analyzed for testosterone content. A mean (SD) of 0.16 (0.46) to 0.65(1.03) µg of residual testosterone (i.e., 99% reduction compared to when hands were not washed) was recovered after washing hands with liquid soap and warm water.

Effect of Showering

The effect of showering (with mild soap) at 1, 2 and 6 hours post application of testosterone gel 100 mg was evaluated in a clinical trial in 12 men. The study demonstrated that the overall effect of washing was to decrease testosterone concentrations; however, when washing occurred two or more hours post drug application, serum testosterone concentrations remained within the normal range.

13 NONCLINICAL TOXICOLOGY

13.1 Carcinogenesis, Mutagenesis, Impairment of Fertility

Carcinogenicity

Testosterone has been tested by subcutaneous injection and implantation in mice and rats. In mice, the implant induced cervical-uterine tumors, which metastasized in some cases. There is suggestive evidence that injection of testosterone into some strains of female mice increases their susceptibility to hepatoma. Testosterone is also known to increase the number of tumors and decrease the degree of differentiation of chemically induced carcinomas of the liver in rats.

Mutagenesis

Testosterone was negative in the in vitroAmes and in the in vivomouse micronucleus assays.

Impairment of Fertility

The administration of exogenous testosterone has been reported to suppress spermatogenesis in the rat, dog and non-human primates, which was reversible on cessation of the treatment.

14 CLINICAL STUDIES

14.1 Clinical Study in Hypogonadal Males

Testosterone gel was evaluated in a randomized multicenter, multi-dose, active and placebo controlled 90-day study in 406 adult males with morning testosterone levels ≤300 ng/dL. The study was double-blind for the doses of testosterone gel and placebo, but open label for the non-scrotal testosterone transdermal system. During the first 60 days, patients were evenly randomized to testosterone gel 50 mg, testosterone gel 100 mg, placebo gel, or testosterone transdermal system. At Day 60, patients receiving testosterone gel were maintained at the same dose, or were titrated up or down within their treatment group, based on 24-hour averaged serum testosterone concentration levels obtained on Day 30.

Of 192 hypogonadal men who were appropriately titrated with testosterone gel and who had sufficient data for analysis, 74% achieved an average serum testosterone level within the normal range (300 to 1,000 ng/dL) on treatment Day 90.

Table 4 summarizes the mean testosterone concentrations on Day 30 for patients receiving testosterone gel 50 mg or 100 mg.

Table 4: Mean (± SD) Steady-State Serum Testosterone Concentrations on Day 30
 | Testosterone gel 50 mg | Testosterone gel 100 mg | Placebo gel
 | n=94 | n=95 | n=93
Cavg(ng/dL) | 365 ± 187 | 612 ± 286 | 216 ± 79
Cmax(ng/dL) | 538 ± 371 | 897 ± 565 | 271 ± 110
Cmin(ng/dL) | 223 ± 126 | 394 ±189 | 164 ± 64

16 HOW SUPPLIED/STORAGE AND HANDLING

16.1 How Supplied

Vogelxo is supplied in unit-dose tubes in cartons of 30 and unit-dose packets in cartons of 30. Each tube or packet contains 50 mg testosterone in 5 g of gel.

Vogelxo is also supplied in a metered-dose pump that delivers 12.5 mg of testosterone per complete pump actuation. Each 88 g metered-dose pump is capable of dispensing 75 g of gel or 60-metered pump actuations. Each pump actuation delivers 1.25 g of gel. The metered-dose pump is supplied in cartons of 2.

Vogelxo is available as follows:

NDC Number | Strength | Package Size
0245-0871-05 | 50 mg of testosterone | 30 tubes (5 g of gel per tube)
0245-0871-65 | 50 mg of testosterone | 1 tube (5 g of gel per tube)
0245-0871-35 | 50 mg of testosterone | 30 packets (5 g of gel per packet)
0245-0871-89 | 50 mg of testosterone | 1 packet (5 g of gel per packet)
0245-0872-42 | 12.5 mg of testosterone per pump actuation | 2 × 75 g pumps (each pump dispenses 60 metered 1.25 g of gel)

16.2 Storage

Store at 20° to 25°C (68° to 77°F); excursions permitted to 15° to 30°C (59° to 86°F). [See USP Controlled Room Temperature.]

16.3 Handling and Disposal

Used Vogelxo tubes, packets or pumps should be discarded in household trash in a manner that prevents accidental exposure of women, children, or pets [see Boxed Warningand Warnings and Precautions (5.2)] . Contents are flammable [see Warnings and Precautions (5.16)] .

17 PATIENT COUNSELING INFORMATION

Advise the patient to read the FDA-approved patient labeling (Medication Guide).

Men with Known or Suspected Carcinoma of the Breast or Prostate

Men with known or suspected prostate or breast cancer should not use Vogelxo [see Contraindications (4)and Warnings and Precautions (5.1)] .

Potential for Secondary Exposure to Testosterone and Steps to Prevent Secondary Exposure

Secondary exposure to testosterone in children and women can occur with the use of testosterone gel products in men. Cases of secondary exposure to testosterone have been reported in children.

Physicians should advise patients of the reported signs and symptoms of secondary exposure which may include the following:

- In children; unexpected sexual development including inappropriate enlargement of the penis or clitoris, premature development of pubic hair, increased erections, and aggressive behavior
- In women; changes in hair distribution, increase in acne, or other signs of testosterone effects
- The possibility of secondary exposure to Vogelxo should be brought to the attention of a healthcare provider
- Vogelxo should be promptly discontinued until the cause of virilization is identified

Strict adherence to the following precautions is advised to minimize the potential for secondary exposure to testosterone from Vogelxo in men [see Medication Guide]

- Children and women should avoid contact with unwashed or unclothed application site(s) of men using Vogelxo
- Patients using Vogelxo should apply the product as directed and strictly adhere to the following:
  - Wash handswith soap and water immediately after application
  - Cover the application site(s)with clothing after the gel has dried
  - Wash the application site(s) thoroughlywith soap and water prior to any situation where skin-to-skin contact of the application site with another person is anticipated
- In the event that unwashed or unclothed skin to which Vogelxo has been applied comes in contact with the skin of another person, the general area of contact on the other person should be washed with soap and water as soon as possible [see Dosage and Administration (2.2), Warnings and Precautions (5.2)and Clinical Pharmacology (12.3)].

Potential Adverse Reactions with Androgens

Patients should be informed that treatment with androgens may lead to adverse reactions which include:

- Changes in urinary habits, such as increased urination at night, trouble starting the urine stream, passing urine many times during the day, having an urge to go the bathroom right away, having a urine accident, or being unable to pass urine or weak urine flow
- Breathing disturbances, including those associated with sleep or excessive daytime sleepiness.
- Too frequent or persistent erections of the penis
- Nausea, vomiting, changes in skin color, or ankle swelling

Patients Should Be Advised of the Following Instructions for Use

- Read the Medication Guide before starting Vogelxo therapy and reread it each time the prescription is renewed.
- Vogelxo should be applied and used appropriately to maximize the benefits and to minimize the risk of secondary exposure in children and women.
- Keep Vogelxo out of the reach of children. The package is not child resistant.
- Vogelxo is an alcohol-based product and is flammable; therefore avoid fire, flame or smoking until the gel has dried.
- It is important to adhere to all recommended monitoring.
- Report any changes in their state of health, such as changes in urinary habits, breathing, sleep, and mood.
- Vogelxo is prescribed to meet the patient's specific needs; therefore, the patient should never share Vogelxo with anyone.
- Vogelxo should be applied topically once daily at approximately the same time each day to clean dry skin of the shoulders and/or upper arms.
- Vogelxo should not be applied to the scrotum, penis, or abdomen.
- Wait 2 hours before washing or swimming following application of Vogelxo. This will ensure that the greatest amount of Vogelxo is absorbed.

Distributed by
UPSHER-SMITH LABORATORIES, LLC
Maple Grove, MN 55369

MADE IN CANADA

Vogelxo is a registered trademark of Upsher-Smith Laboratories, LLC.

Revised 04/2020

MEDICATION GUIDE
VOGELXO®(voh-JELKS-oh) CIII
(testosterone) gel, for topical use

What is the most important information I should know about Vogelxo?

- Vogelxo can transfer from your body to others including, children and women. Children and women should avoid contact with the unwashed or not covered (unclothed areas) where Vogelxo has been applied to your skin. Early signs and symptoms of puberty have occurred in young children who have come in direct contact with testosterone by touching areas where men have used Vogelxo.
  Children
  Signs and symptoms of early puberty in a child when they come in direct contact with Vogelxo may include:
  - Abnormal sexual changes:
    - enlarged penis or clitoris.
    - early growth of hair near the vagina or around the penis (pubic hair).
    - erections or acting out sexual urges (sex drive).
  - Behavior problems:
    - acting aggressively, behaving in an angry or violent way.
  - Women
    Signs and symptoms in women when they come in direct contact with Vogelxo may include:
    - changes in body hair.
    - an abnormal increase in pimples (acne).

Stop using Vogelxo and call your healthcare provider right away if you see any signs and symptomsin a child or a woman that may have happened through accidental touching of the area where you have applied Vogelxo.

- To lower the risk of transfer of Vogelxo from your body to others, follow these important instructions:
  - Apply Vogelxo only to the areas of your shoulders and upper arms that will be covered by a short sleeve t-shirt.
  - Wash your hands right away with soap and water after applying Vogelxo.
  - After the gel has dried, cover the application area with clothing. Keep the area covered until you have washed the application area well or have showered.
  - If you expect to have skin-to-skin contact with another person, first wash the application area well with soap and water.
  - If a child or woman touches the area where you have applied Vogelxo, that area on the child or woman should be washed well with soap and water right away.

What is Vogelxo?
Vogelxo is a prescription medicine that contains testosterone. Vogelxo is used to treat adult males who have low or no testosterone due to certain medical conditions.

- Your healthcare provider will test your blood before you start and while you are using Vogelxo.
- It is not known if Vogelxo is safe or effective to treat men who have low testosterone due to aging.
- It is not known if Vogelxo is safe or effective in children younger than 18 years old. Improper use of Vogelxo may affect bone growth in children.

Vogelxo is a controlled substance (CIII) because it contains testosterone that can be a target for people who abuse prescription medicines. Keep your Vogelxo in a safe place to protect it. Never give your Vogelxo to anyone else, even if they have the same symptoms you have. Selling or giving away this medicine may harm others and it is against the law.
Vogelxo is not meant for use in women.

Do not use Vogelxo if you:

- have breast cancer.
- have or might have prostate cancer.
- are a woman who is pregnant. Vogelxo may harm your unborn baby.
- Women who are pregnant or who may become pregnant should avoid contact with the area of skin where Vogelxo has been applied.

Before using Vogelxo, tell your healthcare provider about all of your medical conditions including if you:

- have breast cancer.
- have or might have prostate cancer.
- have urinary problems due to an enlarged prostate.
- have heart problems.
- have liver or kidney problems.
- have problems breathing while you sleep (sleep apnea).

Tell your healthcare provider about all the medicines you take, including prescription and over-the-counter medicines, vitamins, and herbal supplements. Using Vogelxo with certain other medicines you take can affect each other.
Especially, tell your healthcare provider if you take:

- insulin
- medicines that decrease blood clotting (blood thinners)
- corticosteroids

How should I use Vogelxo?

- See the detailed Instructions for Usefor information about how to use Vogelxo at the end of this Medication Guide.
- It is important that you apply Vogelxo exactly as your healthcare provider tells you to.
- Your healthcare provider may change your Vogelxo dose. Do notchange your Vogelxo dose without talking to your healthcare provider.
- Apply Vogelxo at the same time each day. Vogelxo should be applied after showering or bathing.

What are the possible side effects of Vogelxo?
Vogelxo can cause serious side effects including:
See " What is the most important information I should know about Vogelxo?"

- If you already have enlargement of your prostate gland your signs and symptoms can get worse while using Vogelxo.This can include:
  - increased urination at night.
  - trouble starting your urine stream.
  - having to pass urine many times during the day.
  - having an urge to go to the bathroom right away.
  - having a urine accident.
  - being unable to pass urine or weak urine flow.
- Possible increased risk of prostate cancer.Your healthcare provider should check you for prostate cancer or any other prostate problems before you start and while you use Vogelxo.
- Blood clots in your legs or lungs.Signs and symptoms of a blood clot in your legs can include leg pain, swelling or redness. Signs and symptoms of a blood clot in your lungs can include difficulty breathing or chest pain.
- Possible increased risk of heart attack or stroke.
- In large doses Vogelxo may lower your sperm count.
- Swelling of your ankles, feet, or body, with or without heart failure.
- Enlarged or painful breasts.
- Having problems breathing while you sleep (sleep apnea).

Call your healthcare provider right away if you have any of the serious side effects listed above.
The most common side effects of Vogelxo include:

- skin irritation where Vogelxo is applied
- increased red blood cell count
- headache
- increased blood pressure

Other side effects includemore erections than are normal for you or erections that last a long time.
Tell your healthcare provider if you have any side effect that bothers you or that does not go away.
These are not all the possible side effects of Vogelxo. For more information, ask your healthcare provider or pharmacist.
Call your doctor for medical advice about side effects. You may report side effects to FDA at 1-800-FDA-1088.

General information about the safe and effective use of Vogelxo.
Medicines are sometimes prescribed for purposes other than those listed in a Medication Guide. Do not use Vogelxo for a condition for which it was not prescribed. Do not give Vogelxo to other people, even if they have the same symptoms that you have. It may harm them.
You can ask your pharmacist or healthcare provider for information about Vogelxo that is written for health professionals.

What are the ingredients in Vogelxo?
Active ingredient: testosterone
Inactive ingredients:carbomer copolymer Type B, carbomer homopolymer Type C, diisopropyl adipate, ethyl alcohol, glycerin, methyl laurate, oleyl alcohol, polyethylene glycol, propylene glycol, purified water, and tromethamine
Distributed by
UPSHER-SMITH LABORATORIES, LLC
Maple Grove, MN 55369
MADE IN CANADA
For more information about Vogelxo, call 1-888-650-3789 or go to www.upsher-smith.com

This Medication Guide has been approved by the U.S. Food and Drug Administration.

Revised 4/2020

INSTRUCTIONS FOR USE
VOGELXO®(voh-JELKS-oh), CIII
(testosterone)
gel, for topical use

Read this Instructions for Use for Vogelxo before you start using it and each time you get a refill. There may be new information. This leaflet does not take the place of talking to your healthcare provider about your medical condition or treatment.

Applying Vogelxo:
Vogelxo comes in tubes, packets, or in a pump.

- Before applying Vogelxo, make sure that your shoulders and upper arms are clean, dry, and there is no broken skin.
- The application sites for Vogelxo are the shoulders and the upper arms that will be covered by a short sleeve t-shirt (See Figure A). Do notapply Vogelxo to any other parts of your body such as your penis, scrotum, or stomach area (abdomen).

(Figure A)

If you are using Vogelxo tubes:

- Remove the cap from the tube and use the top of the cap to puncture the metal seal on the top of the tube.
- Squeeze from the bottom of the tube to the top.
- Squeeze all of the Vogelxo out of the tube into the palm of your hand.
- Vogelxo is to be applied only to the areas of your shoulders and upper arms that will be covered by a short sleeve t-shirt.
- Apply Vogelxo to the application site. Rub the gel onto your skin for several seconds.
- Vogelxo is flammable until dry. Let Vogelxo dry before smoking or going near an open flame.
- Let the application site dry for a few minutes before putting on a t-shirt.
- Wash your hands with soap and water right away after applying Vogelxo.
- Put the cap back on the tube.
- Avoid showering, swimming, or bathing for at least 2 hours after you apply Vogelxo.

If you are using Vogelxo packets:

- Tear open the packet completely at the notch on the top edge. Squeeze from the bottom of the packet to the top.
- Squeeze all of the Vogelxo out of the packet into the palm of your hand. Apply Vogelxo to the application site. Rub the gel onto your skin for several seconds.
- Let the application site dry for a few minutes before putting on a t-shirt.
- Wash your hands with soap and water right awayafter applying Vogelxo.

If you are using the Vogelxo pump:

- Before using a new bottle of Vogelxo for the first time, you will need to prime the pump. To prime the Vogelxo pump, remove the cap and slowly push the pump all the way down 3 times.
- Do not use any Vogelxo that came out while priming. Wash it down the sink to avoid accidental exposure to others. Your Vogelxo pump is now ready to use.
- Remove the cap from the pump. Then position the nozzle over the palm of your hand and slowly push the pump all the way down. Your healthcare provider will tell you the number of times to press the pump for each dose.
- Apply Vogelxo to the application site. Rub the gel onto your skin for several seconds.
- Let the application site dry for a few minutes before putting on a t-shirt.
- Wash your hands with soap and water right away.
- Put the cap back on the pump.

How should I store Vogelxo?

- Store Vogelxo at room temperature between 68º to 77ºF (20º to 25ºC).
- Safely throw away used Vogelxo containers in the household trash. Be careful to prevent accidental exposure of children or pets.
- Keep Vogelxo away from fire.

Keep Vogelxo and all medicines out of the reach of children.

This Instructions for Use has been approved by the U.S. Food and Drug Administration Revised:

Revised 4/2020

<

PRINCIPAL DISPLAY PANEL - 50 mg Tube Carton

NDC 0245-0871-05

Vogelxo®
(testosterone) gel
50 mg testosterone per tube

Each unit-dose tube
contains 5 grams of gel.

CIII

For topical use only.

Topical testosterone products may have different doses, strengths,
or application instructions that may result in different systemic exposure.

To be applied to the shoulders and upper arms.

PHARMACIST: Dispense the Medication Guide provided separately
to each patient.

Contains 30 Unit-dose Tubes
Rx only

UPSHER-SMITH

PRINCIPAL DISPLAY PANEL - 12.5 mg Bottle Carton

NDC 0245-0872-42

Vogelxo®
(testosterone) gel
12.5 mg of testosterone
per pump actuation*

*Each actuation delivers
1.25 grams of gel.
Multi-dose pump capable of
dispensing 60 metered
pump actuations.

CIII

For topical use only.

Topical testosterone products may have different
doses, strengths, or application instructions that
may result in different systemic exposure.

To be applied to the shoulders and upper arms.

PHARMACIST: Dispense the Medication Guide
provided separately to each patient.

2 canisters containing 88 grams each
Rx only

UPSHER-SMITH